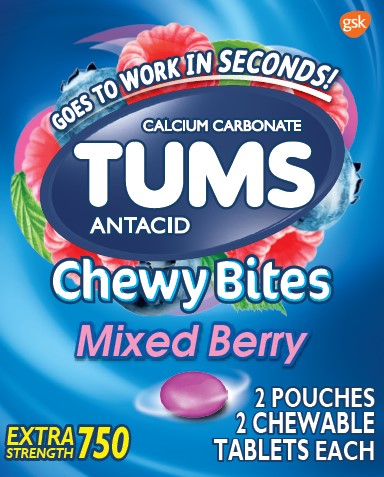 DRUG LABEL: TUMS CHEWY BITES
NDC: 29485-8120 | Form: TABLET, CHEWABLE
Manufacturer: Lil' Drug Store Products, Inc.
Category: otc | Type: HUMAN OTC DRUG LABEL
Date: 20240329

ACTIVE INGREDIENTS: CALCIUM CARBONATE 750 mg/1 1
INACTIVE INGREDIENTS: MALTODEXTRIN; CARMINIC ACID; COCONUT OIL; CITRIC ACID MONOHYDRATE; FD&C BLUE NO. 1; SOYBEAN OIL; ICODEXTRIN; LECITHIN, SOYBEAN; SUCROSE; TITANIUM DIOXIDE; ETHYL ACETATE; ALUMINUM OXIDE; FD&C RED NO. 40; FD&C YELLOW NO. 6; METHYLPARABEN; BUTYL ALCOHOL; PROPYLENE GLYCOL; SORBITOL; CORN OIL; AMMONIA; ACACIA; ALCOHOL; YELLOW WAX; CARNAUBA WAX; STARCH, CORN; CORN SYRUP; ISOPROPYL ALCOHOL; PHOSPHORIC ACID; SHELLAC; SORBIC ACID; PROPYLPARABEN; WATER; TERT-BUTYLHYDROQUINONE; FD&C BLUE NO. 2

TUMS CHEWY BITES- calcium carbonate tablet, chewable

Active Ingredient (per tablet)

Calcium Carbonate USP 750mg

Purpose

Antacid

USES

relieves

- heartburn
- acid indigestion
- sour stomach
- upset stomach associated with these symptoms

Warnings

Ask a doctor or pharmacist before use if you are

presently taking a prescription drug. Antacids may interact with certain prescription drugs.

When using this product

- do not take more than 6 tablets in 24 hours
- if pregnant do not take more than 6 tablets in 24 hours
- do not use the maximum dosage for more than 2 weeks except under the advice and supervision of a doctor

Directions

- adults and children 12 years of age and over: chew 2-4 tablets as symptoms occur, or as directed by a doctor

- do not take for symptoms that persist for more than 2 weeks unless advised by a doctor

Other Information

- each chewable tablet contains: elemental calcium 300mg
- do not store above 25°C (77°F)

Inactive Ingredients

Acacia gum, alcohol, ammonium hydroxide, beeswax, carmine, carnauba wax, citric acid, coconut oil, corn starch, corn syrup, dextrin, ethyl acetate, ethyl alcohol, FD&C blue #1 alum lake, FD&C blue #2 alum lake, FD&C red #40 alum lake, FD&C yellow #6 alum lake, flavors, gum arabic, isopropyl alcohol, maltodextrin, methylparaben, n-butyl alcohol, phosphoric acid, propylparaben, propylene glycol, purified water, shellac, sorbic acid, sorbitol, soybean oil, soy lecithin, sucrose, TBHQ, titanium dioxide, vegetable oil

Questions?

Call 1-800-897-7535

*This product is not manufactured or distributed by GSK Consumer Healthcare

Repackaged and Distributed with Permission of the Manufacturer by : Lil’ Drug Store Products, Inc., Cedar Rapids, IA 52404

TUMS® Chewy Bites 4 Count Carton

GOES TO WORK IN SECONDS!

TUMS®

CALCIUM CARBONATE

ANTACID

Chewy Bites

Mixed Berry

EXTRA STRENGTH 750

2 POUCHES

2 CHEWABLE

TABLETS EACH